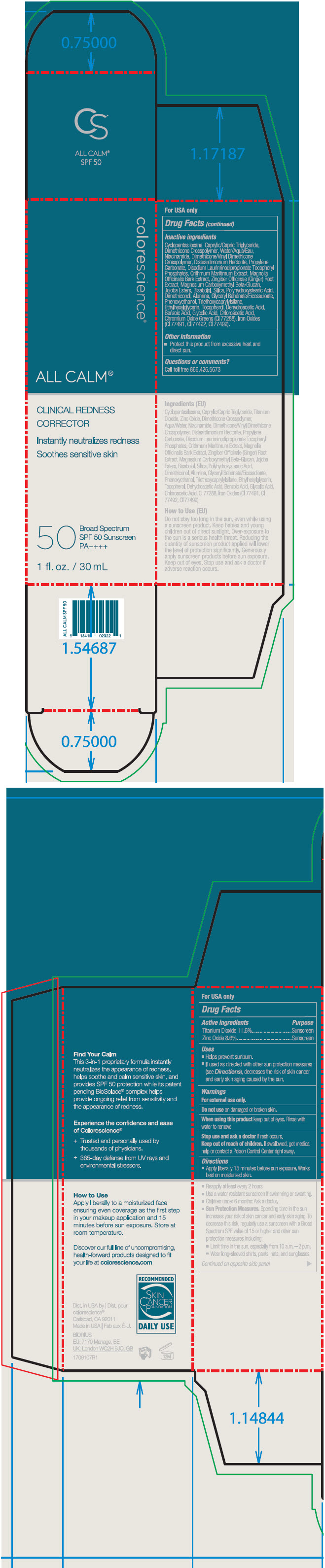 DRUG LABEL: All Calm Clinical Redness Corrector SPF 50
NDC: 68078-023 | Form: LIQUID
Manufacturer: Colorescience
Category: otc | Type: HUMAN OTC DRUG LABEL
Date: 20241212

ACTIVE INGREDIENTS: Titanium Dioxide 116 mg/1 mL; Zinc Oxide 86 mg/1 mL
INACTIVE INGREDIENTS: CYCLOMETHICONE 5; MEDIUM-CHAIN TRIGLYCERIDES; WATER; DIMETHICONE CROSSPOLYMER (450000 MPA.S AT 12% IN CYCLOPENTASILOXANE); Niacinamide; Disteardimonium Hectorite; DIMETHICONE/VINYL DIMETHICONE CROSSPOLYMER (SOFT PARTICLE); FERRIC OXIDE YELLOW; Propylene Carbonate; DISODIUM LAURIMINODIPROPIONATE TOCOPHERYL PHOSPHATES; CHROMIC OXIDE; ALUMINUM OXIDE; SILICON DIOXIDE; DIMETHICONOL (100000 CST); CYCLOMETHICONE 4; JOJOBA OIL; POLYHYDROXYSTEARIC ACID STEARATE; Glyceryl Behenate/Eicosadioate; LEVOMENOL; FERRIC OXIDE RED; Phenoxyethanol; CRITHMUM MARITIMUM WHOLE; Triethoxycaprylylsilane; ETHYLHEXYLGLYCERIN; Tocopherol; MAGNOLIA OFFICINALIS BARK; Benzoic Acid; GINGER; Dehydroacetic Acid; Glycolic Acid; Chloroacetic Acid

All Calm™ Clinical Redness Corrector SPF 50

Drug Facts

ACTIVE INGREDIENT

Active ingredients | Purpose
Titanium Dioxide 11.6% | Sunscreen
Zinc Oxide 8.6% | Sunscreen

Uses

- Helps prevent sunburn.
- If used as directed with other sun protection measures (see Directions), decreases the risk of skin cancer and early skin aging caused by the sun.

Warnings

For external use only.

Do not use on damaged or broken skin.

When using this product keep out of eyes. Rinse with water to remove.

Stop use and ask a doctor if rash occurs.

Keep out of reach of children. If swallowed, get medical help or contact a Poison Control Center right away.

Directions

- Apply liberally 15 minutes before sun exposure. Works best on moisturized skin.
- Reapply at least every 2 hours.
- Use a water resistant sunscreen if swimming or sweating.
- Children under 6 months: Ask a doctor.
- Sun Protection Measures. Spending time in the sun increases your risk of skin cancer and early skin aging. To decrease this risk, regularly use a sunscreen with a Broad Spectrum SPF value of 15 or higher and other sun protection measures including:
  - Limit time in the sun, especially from 10 a.m. – 2 p.m.
  - Wear long-sleeved shirts, pants, hats, and sunglasses.

Inactive ingredients

Cyclopentasiloxane, Caprylic/Capric Triglyceride, Water/Aqua/Eau, Dimethicone Crosspolymer, Niacinamide, Disteardimonium Hectorite, Dimethicone/Vinyl Dimethicone Crosspolymer, Propylene Carbonate, Disodium Lauriminodipropionate Tocopheryl Phosphates, Crithmum Maritimum Extract, Magnolia Officinalis Bark Extract, Zingiber Officinale (Ginger) Root Extract, Magnesium Carboxymethyl Beta-Glucan, Jojoba Esters, Bisabolol, Silica, Polyhydroxystearic Acid, Dimethiconol, Alumina, Glyceryl Behenate/Eicosadioate, Phenoxyethanol, Triethoxycaprylylsilane, Ethylhexylglycerin, Tocopherol, Dehydroacetic Acid, Benzoic Acid, Glycolic Acid, Chloroacetic Acid, Chromium Oxide Greens (CI 77288), Iron Oxides (CI 77491, CI 77492, CI 77499).

Other information

- Protect this product from excessive heat and direct sun.

Questions or comments?

Call toll free 866.426.5673

Dist. in USA by
colorescience®
Carlsbad, CA 92011

PRINCIPAL DISPLAY PANEL - 30 mL Tube Carton

colorescience®

ALL CALM™

CLINICAL REDNESS
CORRECTOR

Instantly neutralizes redness
Soothes sensitive skin

50
Broad Spectrum
SPF 50 Sunscreen
PA++++

1 fl. oz. / 30 mL